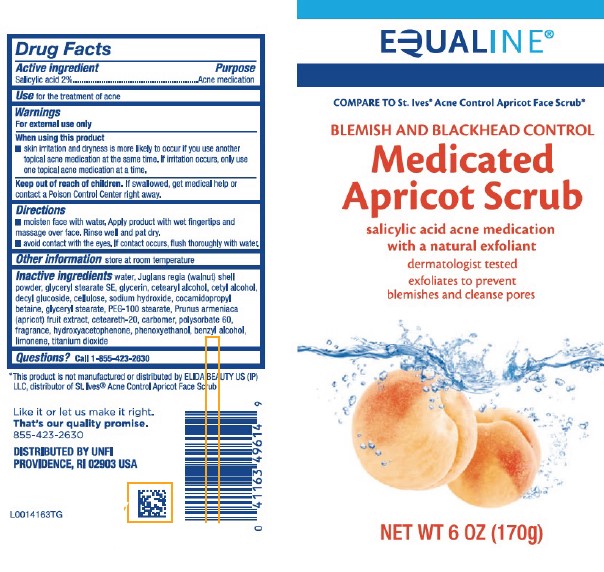 DRUG LABEL: Medicated Apricot Scrub
NDC: 41163-041 | Form: GEL
Manufacturer: United Natural Foods, Inc. dba UNFI
Category: otc | Type: HUMAN OTC DRUG LABEL
Date: 20260216

ACTIVE INGREDIENTS: SALICYLIC ACID 20 mg/1 g
INACTIVE INGREDIENTS: JUGLANS REGIA SHELL; GLYCERYL STEARATE SE; GLYCERIN; CETOSTEARYL ALCOHOL; CETYL ALCOHOL; DECYL GLUCOSIDE; POWDERED CELLULOSE; SODIUM HYDROXIDE; COCAMIDOPROPYL BETAINE; GLYCERYL MONOSTEARATE; PEG-100 STEARATE; APRICOT; POLYOXYL 20 CETOSTEARYL ETHER; WATER; CARBOMER HOMOPOLYMER, UNSPECIFIED TYPE; POLYSORBATE 60; HYDROXYACETOPHENONE; PHENOXYETHANOL; BENZYL ALCOHOL; LIMONENE, (+)-; TITANIUM DIOXIDE

Equaline 041.008/041AM
Medicated Apricot Scrub

Active ingredient

Salicylic acid 2%

Purpose

Acne medication

Use

for the treatment of acne

Warnings

For external use only

When using this product

- skin irritation and dryness is more likely to occure if you use another topical acne medication at the same time. If irritation occurs, only use one topical acne medication at a time.

Keep out of reach of children.

If swallowed, get medical help or contact a Poison Control Center right away.

Directions

- moisten face with water. Apply product with wet fingertips and masage over face. Rinse well and pat dry.
- avoid contact with the eyes. If contact occurs, flush thoroughly with water.

Other information

store at room temperature

Inactive ingredients

water, Juglans regia (walnut) shell powder, glyceryl stearate SE, glycerin, cetearyl alcohol, cetyl alcohol, decyl glucoside, cellulose, sodium hydroxide, cocamidopropyl betaine, glyceryl stearate, PEG-100 stearate, Prunus armeniaca (apricot) fruit extract, ceteareth-20, carbomer, polysorbate 60, fragrance, hydroxyacetophenone, phenoxyethanol, benzyl alcohol, limonene, titanium dioxide

Questions?

Call 1-855-423-2630

Disclaimer

*This product is not manufactured or distributed by ELIDA BEAUTY US (IP) LLC, distributor of St. Ives® Acne Control Apricot Face Scrub.

Adverse reaction

Like it or let us make it right.

That's our quality promise.

855-423-2630

DISTRIBUTED BY UNFI

PROVIDENCE, RI 02908 USA

Principal Panel Display

EQUALINE®

COMPARE TO St. Ives®Acne Control Apricot Face Scrub*

BLEMISH AND BLACKHEAD CONTROL

Medicated Apricot Scrub

salicylic acid acne medication with a natural exfoliant

dermatologist tested

exfoliates to prevent blemishes and cleanse pores

NET WT 6 0Z (170 g)